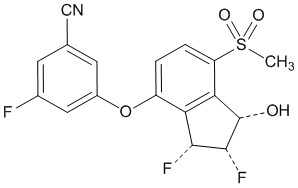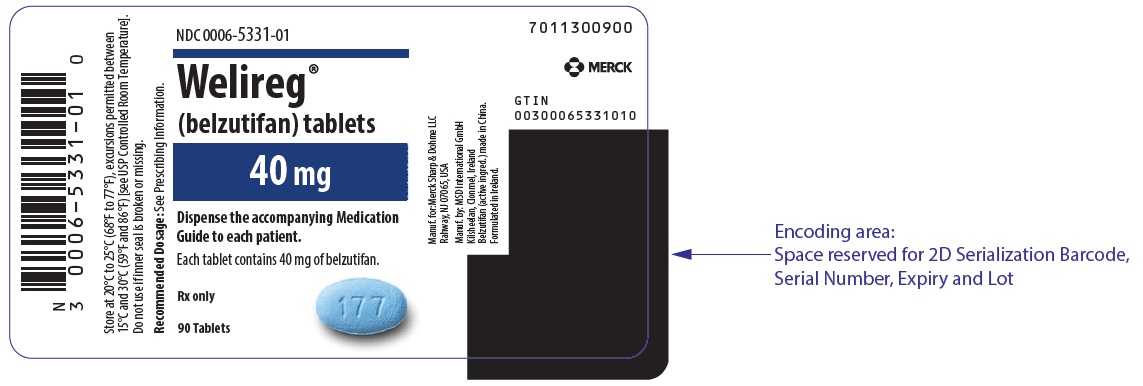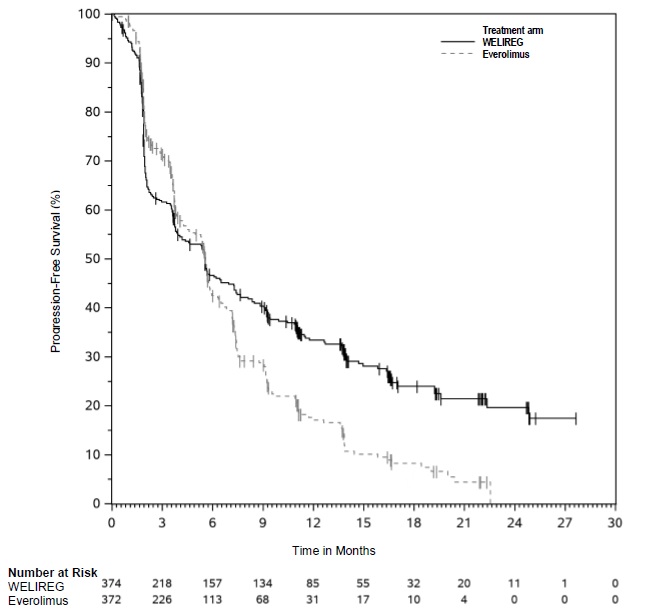 DRUG LABEL: WELIREG
NDC: 0006-5331 | Form: TABLET, FILM COATED
Manufacturer: Merck Sharp & Dohme LLC
Category: prescription | Type: HUMAN PRESCRIPTION DRUG LABEL
Date: 20250514

ACTIVE INGREDIENTS: BELZUTIFAN 40 mg/1 1
INACTIVE INGREDIENTS: CROSCARMELLOSE SODIUM; HYPROMELLOSE ACETATE SUCCINATE 06081224 (3 MPA.S); MAGNESIUM STEARATE; MANNITOL; MICROCRYSTALLINE CELLULOSE; SILICON DIOXIDE; FD&C BLUE NO. 2 ALUMINUM LAKE; POLYETHYLENE GLYCOL, UNSPECIFIED; POLYVINYL ALCOHOL, UNSPECIFIED; TALC; TITANIUM DIOXIDE

HIGHLIGHTS OF PRESCRIBING INFORMATION

These highlights do not include all the information needed to use WELIREG safely and effectively. See full prescribing information for WELIREG.
WELIREG® (belzutifan) tablets, for oral use
Initial U.S. Approval: 2021

WARNING: EMBRYO-FETAL TOXICITY

See full prescribing information for complete boxed warning.

- Exposure to WELIREG during pregnancy can cause embryo-fetal harm.
- Verify pregnancy status prior to the initiation of WELIREG.
- Advise patients of these risks and the need for effective non-hormonal contraception. WELIREG can render some hormonal contraceptives ineffective. (5.3, 7.2, 8.1, 8.3)

RECENT MAJOR CHANGES

Indications and Usage, Advanced Renal Cell Carcinoma (RCC),
Pheochromocytoma or Paraganglioma (PPGL) (1.3) | 05/2025
Recommended Dosage (2.1) | 05/2025
Warnings and Precautions (5.1, 5.2) | 05/2025

1 INDICATIONS AND USAGE

WELIREG is a hypoxia-inducible factor inhibitor indicated:

von Hippel-Lindau (VHL) disease

- for treatment of adult patients with von Hippel-Lindau (VHL) disease who require therapy for associated renal cell carcinoma (RCC), central nervous system (CNS) hemangioblastomas, or pancreatic neuroendocrine tumors (pNET), not requiring immediate surgery. (1.1)

Advanced Renal Cell Carcinoma (RCC)

- for treatment of adult patients with advanced renal cell carcinoma (RCC) with a clear cell component following a programmed death receptor-1 (PD-1) or programmed death-ligand 1 (PD-L1) inhibitor and a vascular endothelial growth factor tyrosine kinase inhibitor (VEGF-TKI). (1.2)

Pheochromocytoma or Paraganglioma (PPGL)

- for treatment of adult and pediatric patients 12 years and older with locally advanced, unresectable, or metastatic pheochromocytoma or paraganglioma (PPGL). (1.3)

2 DOSAGE AND ADMINISTRATION

The recommended dosage of WELIREG in adult patients is 120 mg administered orally once daily with or without food. (2.1)

The recommended dosage of WELIREG in pediatric patients 12 years and older is based on bodyweight:

- Patients weighing ≥ 40 kg: 120 mg orally once daily
- Patients weighing < 40 kg: 80 mg orally once daily

3 DOSAGE FORMS AND STRENGTHS

Tablets: 40 mg (3)

4 CONTRAINDICATIONS

None. (4)

5 WARNINGS AND PRECAUTIONS

- Anemia: Monitor for anemia before initiation of and periodically throughout treatment with WELIREG. Withhold WELIREG until hemoglobin ≥8g/dL, then resume at the same or reduced dose or discontinue. For life threatening anemia, or for anemia requiring urgent intervention, withhold WELIREG until hemoglobin ≥8g/dL and resume at a reduced dose or permanently discontinue WELIREG. (2.2, 5.1)
- Hypoxia: Monitor oxygen saturation before initiation of, and periodically throughout, treatment with WELIREG. For hypoxia at rest, withhold until resolved, resume at reduced dose, or discontinue depending on severity. For life-threatening hypoxia, permanently discontinue WELIREG. (2.2, 5.2)

6 ADVERSE REACTIONS

VHL disease: Most common (≥25%) adverse reactions, including laboratory abnormalities, were decreased hemoglobin, fatigue, increased creatinine, headache, dizziness, increased glucose, and nausea. (6.1)

Advanced RCC: Most common (≥25%) adverse reactions, including laboratory abnormalities were decreased hemoglobin, fatigue, musculoskeletal pain, increased creatinine, decreased lymphocytes, increased alanine aminotransferase, decreased sodium, increased potassium, and increased aspartate aminotransferase. (6.1)

PPGL: Most common (≥25%) adverse reactions, including laboratory abnormalities were anemia, fatigue, musculoskeletal pain, decreased lymphocytes, increased alanine aminotransferase, increased aspartate aminotransferase, increased calcium, dyspnea, increased potassium, decreased leukocytes, headache, increased alkaline phosphatase, dizziness, and nausea. (6.1)

To report SUSPECTED ADVERSE REACTIONS, contact Merck Sharp & Dohme LLC at 1-877-888-4231 or FDA at 1-800-FDA-1088 or www.fda.gov/medwatch.

7 DRUG INTERACTIONS

UGT2B17 or CYP2C19 Inhibitors: Monitor for signs and symptoms of anemia and hypoxia and reduce the dosage of WELIREG as recommended. (2.2, 7.1)

8 USE IN SPECIFIC POPULATIONS

- Lactation: Advise not to breastfeed. (8.2)
- Infertility: May impair fertility in males and females. (8.3)

FULL PRESCRIBING INFORMATION

WARNING: EMBRYO-FETAL TOXICITY

- Exposure to WELIREG during pregnancy can cause embryo-fetal harm.
- Verify pregnancy status prior to the initiation of WELIREG.
- Advise patients of these risks and the need for effective non-hormonal contraception. WELIREG can render some hormonal contraceptives ineffective [see Warnings and Precautions (5.3), Drug Interactions (7.2), Use in Specific Populations (8.1, 8.3)].

1 INDICATIONS AND USAGE

1.1 von Hippel-Lindau (VHL) disease

WELIREG is indicated for treatment of adult patients with von Hippel-Lindau (VHL) disease who require therapy for associated renal cell carcinoma (RCC), central nervous system (CNS) hemangioblastomas, or pancreatic neuroendocrine tumors (pNET), not requiring immediate surgery.

1.2 Advanced Renal Cell Carcinoma (RCC)

WELIREG is indicated for the treatment of adult patients with advanced renal cell carcinoma (RCC) with a clear cell component following a programmed death receptor-1 (PD-1) or programmed death-ligand 1 (PD-L1) inhibitor and a vascular endothelial growth factor tyrosine kinase inhibitor (VEGF-TKI).

1.3 Pheochromocytoma or Paraganglioma (PPGL)

WELIREG is indicated for the treatment of adult and pediatric patients 12 years and older with locally advanced, unresectable, or metastatic pheochromocytoma or paraganglioma (PPGL).

2 DOSAGE AND ADMINISTRATION

2.1 Recommended Dosage

The recommended dosage of WELIREG in adult patients is 120 mg administered orally once daily.

The recommended dosage of WELIREG in pediatric patients 12 years and older is based on bodyweight:

- Patients weighing ≥ 40 kg: 120 mg orally once daily
- Patients weighing < 40 kg: 80 mg orally once daily

Continue WELIREG until disease progression or unacceptable toxicity.

WELIREG should be taken at the same time each day and may be taken with or without food.

Advise patients to swallow tablets whole. Do not chew, crush, or split WELIREG prior to swallowing.

If a dose of WELIREG is missed, it can be taken as soon as possible on the same day. Resume the regular daily dose schedule for WELIREG the next day. Do not take extra tablets to make up for the missed dose.

If vomiting occurs any time after taking WELIREG, do not retake the dose. Take the next dose on the next day.

2.2 Dosage Modifications for Adverse Reactions

Dosage modifications for WELIREG for adverse reactions are summarized in Table 1.

The recommended dose reductions are:

- First dose reduction: WELIREG 80 mg orally once daily
- Second dose reduction: WELIREG 40 mg orally once daily
- Third dose reduction: Permanently discontinue

Table 1: Recommended Dosage Modifications for Adverse Reactions
Adverse Reaction | Severity | Dosage Modification
Anemia [see Warnings and Precautions (5.1)] | Hemoglobin <8 g/dL or transfusion indicated | - Withhold until hemoglobin ≥8g/dL. - Resume at the same or reduced dose; or discontinue depending on the severity of anemia.
Anemia [see Warnings and Precautions (5.1)] | Life-threatening or urgent intervention indicated | - Withhold until hemoglobin ≥8g/dL. - Resume at a reduced dose or permanently discontinue.
Hypoxia [see Warnings and Precautions (5.2)] | Decreased oxygen saturation with exercise (e.g., pulse oximeter <88%) | - Consider withholding until resolved. - Resume at the same dose or at a reduced dose depending on the severity of hypoxia.
Hypoxia [see Warnings and Precautions (5.2)] | Decreased oxygen saturation at rest (e.g., pulse oximeter <88% or PaO2 ≤55 mm Hg) or urgent intervention indicated | - Withhold until resolved. - Resume at reduced dose or discontinue depending on the severity of hypoxia.
Hypoxia [see Warnings and Precautions (5.2)] | Life-threatening or recurrent symptomatic hypoxia | - Permanently discontinue.
Other Adverse Reactions [see Adverse Reactions (6)] | Grade 3 | - Withhold dosing until resolved to ≤ Grade 2. - Consider resuming at a reduced dose (reduce by 40 mg). - Permanently discontinue upon recurrence of Grade 3.
Other Adverse Reactions [see Adverse Reactions (6)] | Grade 4 | - Permanently discontinue.

3 DOSAGE FORMS AND STRENGTHS

Tablets: 40 mg, blue, oval shaped, film-coated, debossed with “177” on one side and plain on the other side.

4 CONTRAINDICATIONS

None.

5 WARNINGS AND PRECAUTIONS

5.1 Anemia

WELIREG can cause severe anemia that can require blood transfusion.

Monitor for anemia before initiation of, and periodically throughout, treatment with WELIREG. Transfuse patients as clinically indicated. For patients with hemoglobin <8g/dL, withhold WELIREG until ≥8g/dL, then resume at the same or reduced dose or permanently discontinue WELIREG, depending on the severity of anemia. For life threatening anemia or when urgent intervention is indicated, withhold WELIREG until hemoglobin ≥8g/dL, then resume at a reduced dose or permanently discontinue WELIREG [see Dosage and Administration (2.2)].

von Hippel-Lindau (VHL) disease

In LITESPARK-004, decreased hemoglobin occurred in 93% of patients and 7% had Grade 3 events [see Adverse Reactions (6.1)]. Median time to onset of anemia was 31 days (range: 1 day to 8.4 months).

The safety of erythropoiesis stimulating agents (ESAs) for treatment of anemia in patients with VHL disease treated with WELIREG has not been established. Randomized controlled trials in patients with cancer receiving myelosuppressive chemotherapy with ESAs have shown that ESAs increased the risks of death and serious cardiovascular reactions, and decreased progression-free survival and/or overall survival. See the prescribing information for ESAs for more information.

Advanced Renal Cell Carcinoma (RCC)

In LITESPARK-005, decreased hemoglobin occurred in 88% of patients and 29% had Grade 3 events [see Adverse Reactions (6.1)]. Median time to onset of anemia was 29 days (range: 1 day to 16.6 months). Of the patients with anemia, 22% received transfusions only, 20% of patients received ESAs only and 12% received both transfusion and ESAs.

Pheochromocytoma or Paraganglioma (PPGL)

In LITESPARK-015, anemia occurred in 96% of patients and 22% had Grade 3 events [see Adverse Reactions (6.1)]. Median time to onset of anemia was 29 days (range: 1 day to 22.1 months). Of the patients with anemia, 20% received transfusions only, 26% received ESAs only, and 6% received both transfusion and ESAs.

5.2 Hypoxia

WELIREG can cause severe hypoxia that may require discontinuation, supplemental oxygen, or hospitalization [see Dosage and Administration (2.2)].

Monitor oxygen saturation before initiation of, and periodically throughout, treatment with WELIREG. For decreased oxygen saturation with exercise (e.g., pulse oximeter <88% or PaO2 ≤55 mm Hg), consider withholding WELIREG until pulse oximetry with exercise is greater than 88%, then resume at the same dose or at a reduced dose. For decreased oxygen saturation at rest (e.g., pulse oximeter <88% or PaO2 ≤55 mm Hg) or urgent intervention indicated, withhold WELIREG until resolved and resume at a reduced dose or discontinue. For life-threatening hypoxia or for recurrent symptomatic hypoxia, permanently discontinue WELIREG [see Dosage and Administration (2.2)].

Advise patients to report signs and symptoms of hypoxia immediately to a healthcare provider.

von Hippel-Lindau (VHL) disease

In LITESPARK- 004, hypoxia occurred in 1.6% of patients [see Adverse Reactions (6.1)].

Advanced Renal Cell Carcinoma (RCC)

In LITESPARK- 005, hypoxia occurred in 15% of patients and 10% had Grade 3 events [see Adverse Reactions (6.1)]. Of the patients with hypoxia, 69% were treated with oxygen therapy. Median time to onset of hypoxia was 30.5 days (range: 1 day to 21.1 months).

Pheochromocytoma or Paraganglioma (PPGL)

In LITESPARK-015, hypoxia occurred in 13% of patients and 10% had Grade 3 hypoxia [see Adverse Reactions (6.1)]. Median time to onset of hypoxia was 35 days (range: 6 days to 23.9 months). Of the patients with hypoxia, 67% were treated with oxygen therapy.

5.3 Embryo-Fetal Toxicity

Based on findings in animals, WELIREG can cause fetal harm when administered to a pregnant woman. In an animal reproduction study, oral administration of belzutifan to pregnant rats during the period of organogenesis caused embryo-fetal lethality, reduced fetal body weight, and fetal skeletal malformations at maternal exposures ≥0.2 times the human exposures (AUC) at the recommended dose of 120 mg daily.

Advise pregnant women and females of reproductive potential of the potential risk to the fetus. Advise females of reproductive potential to use effective non-hormonal contraception during treatment with WELIREG and for 1 week after the last dose, since WELIREG can render some hormonal contraceptives ineffective [see Drug Interactions (7.1)]. Advise male patients with female partners of reproductive potential to use effective contraception during treatment with WELIREG and for 1 week after the last dose [see Use in Specific Populations (8.1, 8.3)].

6 ADVERSE REACTIONS

The following clinically significant adverse reactions are discussed elsewhere in the labeling:

- Anemia [see Warnings and Precautions (5.1)]
- Hypoxia [see Warnings and Precautions (5.2)]

6.1 Clinical Trials Experience

Because clinical trials are conducted under widely varying conditions, adverse reaction rates observed in the clinical trials of a drug cannot be directly compared to rates in the clinical trials of another drug and may not reflect the rates observed in practice.

von Hippel-Lindau (VHL) disease

LITESPARK-004

The safety of WELIREG was evaluated in an open-label clinical trial (LITESPARK-004) in 61 patients with VHL disease who had at least one measurable solid tumor localized to the kidney [see Clinical Studies (14.1)]. Patients received WELIREG 120 mg orally once daily until disease progression or unacceptable toxicity. The median duration of exposure to WELIREG was 68 weeks (range: 8.4 to 104.7 weeks).

Serious adverse reactions occurred in 15% of patients who received WELIREG, including anemia, hypoxia, anaphylaxis reaction, retinal detachment, and central retinal vein occlusion (1 patient each).

Permanent discontinuation of WELIREG due to adverse reactions occurred in 3.3% of patients. Adverse reactions which resulted in permanent discontinuation of WELIREG were dizziness and opioid overdose (1.6% each).

Dosage interruptions of WELIREG due to an adverse reaction occurred in 39% of patients. Adverse reactions which required dosage interruption in >2% of patients were fatigue, decreased hemoglobin, anemia, nausea, abdominal pain, headache, and influenza-like illness.

Dose reductions of WELIREG due to an adverse reaction occurred in 13% of patients. The most frequently reported adverse reaction which required dose reduction was fatigue (7%).

The most common (≥25%) adverse reactions, including laboratory abnormalities, that occurred in patients who received WELIREG were decreased hemoglobin, fatigue, increased creatinine, headache, dizziness, increased glucose, and nausea.

Table 2 summarizes the adverse reactions reported in patients treated with WELIREG in LITESPARK-004.

Table 2: Adverse Reactions Occurring in ≥10% of Patients Who Received WELIREG in LITESPARK-004
Adverse Reaction | WELIREG (n=61)
Adverse Reaction | All Grades [Graded per NCI CTCAE v4.0] (%) | Grade 3-4 (%)
General
Fatigue [Includes other related terms] | 64 | 5
Nervous system
Headache | 39 | 0
Dizziness | 38 | 0
Gastrointestinal
Nausea | 31 | 0
Constipation | 13 | 0
Abdominal pain | 13 | 0
Eye Disorders
Visual impairment [Includes visual impairment, vision blurred, central retinal vein occlusion and retinal detachment] | 21 | 3.3
Infections
Upper respiratory tract infection | 21 | 0
Respiratory, Thoracic and Mediastinal
Dyspnea | 20 | 1.6
Musculoskeletal and Connective Tissue
Arthralgia | 18 | 0
Myalgia | 16 | 0
Vascular
Hypertension | 13 | 3.3
Metabolism and Nutrition
Weight increased | 12 | 1.6

Table 3 summarizes the laboratory abnormalities in LITESPARK-004.

Table 3: Select Laboratory Abnormalities (≥10%) That Worsened from Baseline in Patients Who Received WELIREG in LITESPARK-004
Laboratory Abnormality [The denominator used to calculate the rate is based on all patients in the safety analysis population.] | WELIREG (n=61)
Laboratory Abnormality [The denominator used to calculate the rate is based on all patients in the safety analysis population.] | Grades 1-4 % | Grades 3-4 %
Hematology
Decreased hemoglobin | 93 | 7
Decreased leukocytes | 11 | 0
Chemistry
Increased creatinine | 64 | 0
Increased glucose | 34 | 4.9
Increased ALT | 20 | 0
Increased AST | 16 | 0
Decreased calcium (corrected) | 10 | 0
Decreased phosphate | 10 | 1.6

Advanced Renal Cell Carcinoma (RCC)

LITESPARK-005

The safety of WELIREG was evaluated in a randomized, active-controlled study (LITESPARK- 005) in 732 patients with advanced RCC with a clear cell component that has progressed after prior PD-1 or PD-L1 checkpoint inhibitor and VEGF receptor targeted therapies [see Clinical Studies (14.2)]. Patients received 120 mg WELIREG (n=372) or 10 mg everolimus (n=360) orally once daily until disease progression or unacceptable toxicity. The median duration of exposure to WELIREG was 7.6 months (range 0.1 to 28.5 months).

Serious adverse reactions occurred in 38% of patients who received WELIREG. Serious adverse reactions in ≥2% of patients treated with WELIREG were hypoxia (7%), anemia (5%), pneumonia (3.5%), hemorrhage (3%), and pleural effusion (2.2%). Fatal adverse reactions occurred in 3.2% of patients who received WELIREG, including sepsis (0.5%) and hemorrhage (0.5%).

Permanent discontinuation of WELIREG due to adverse reactions occurred in 6% of patients. Adverse reactions which resulted in permanent discontinuation (≥0.5%) of WELIREG were hypoxia (1.1%), anemia (0.5%), and hemorrhage (0.5%).

Dosage interruptions of WELIREG due to an adverse reaction occurred in 39% of patients. Adverse reactions which required dosage interruption in ≥2% of patients were anemia (8%), hypoxia (5%), COVID-19 (4.3%), fatigue (3.2%), and hemorrhage (2.2%).

Dose reductions of WELIREG due to an adverse reaction occurred in 13% of patients. Adverse reactions which required dose reduction in ≥1% of patients were hypoxia (5%) and anemia (3.2%).

The most common (≥25%) adverse reactions, including laboratory abnormalities, that occurred in patients who received WELIREG were decreased hemoglobin, fatigue, musculoskeletal pain, increased creatinine, decreased lymphocytes, increased alanine aminotransferase, decreased sodium, increased potassium, and increased aspartate aminotransferase.

Table 4 summarizes the adverse reactions in LITESPARK-005.

Table 4: Adverse Reactions (≥10%) in Patients with Advanced RCC Receiving WELIREG in LITESPARK-005
Adverse Reaction | WELIREG (n=372) |  | Everolimus (n=360)
Adverse Reaction | All Grades [Graded per NCI CTCAE v5.0] (%) | Grade 3-4 (%) | All Grades (%) | Grade 3-4 (%)
General
Fatigue [Includes other related terms] | 43 | 3.2 | 41 | 6
Edema | 20 | 0.5 | 23 | 0.6
Musculoskeletal and Connective Tissue
Musculoskeletal Pain | 34 | 1.1 | 27 | 2.2
Gastrointestinal
Nausea | 17 | 0.5 | 11 | 0.3
Constipation | 15 | 0 | 8 | 0
Vomiting | 11 | 0.8 | 8 | 0.8
Diarrhea | 11 | 1.3 | 19 | 1.4
Abdominal Pain | 10 | 0.8 | 8 | 0.3
Respiratory, Thoracic, and Mediastinal
Dyspnea | 16 | 1.6 | 16 | 2.5
Hypoxia | 15 | 10 | 1.4 | 1.4
Metabolism and Nutrition
Decreased Appetite | 13 | 1.1 | 16 | 0
Nervous Systems
Headache | 12 | 0.5 | 8 | 0.3
Dizziness | 11 | 0 | 1.9 | 0

Clinically relevant adverse reactions in <10% of patients who received WELIREG in LITESPARK-005 included hemorrhage (9%) [including intracranial/cerebral hemorrhage (0.8%)], rash (8%), hypertension (6%), visual impairment [including vision blurred (4%), visual acuity decreased (1.1%), visual impairment (0.5%), and retinal detachment (0.3%)] (6%) and increased weight (5%).

Table 5 summarizes the laboratory abnormalities in LITESPARK-005.

Table 5: Select Laboratory Abnormalities (≥20%) That Worsened from Baseline In Patients with Advanced RCC who Received WELIREG in LITESPARK-005
Laboratory Test [Each test incidence is based on the number of patients who had both baseline and at least one on-study laboratory measurement available WELIREG (range: 359 to 366 patients), and everolimus (range: 351 to 356 patients).] | WELIREG |  | Everolimus
Laboratory Test [Each test incidence is based on the number of patients who had both baseline and at least one on-study laboratory measurement available WELIREG (range: 359 to 366 patients), and everolimus (range: 351 to 356 patients).] | All Grades [Graded per NCI CTCAE v5.0] % | Grades 3-4 % | All Grades % | Grades 3-4 %
Hematology
Decreased hemoglobin | 88 | 29 | 76 | 17
Decreased lymphocytes | 34 | 8 | 53 | 20
Chemistry
Increased creatinine | 34 | 4.7 | 43 | 5.1
Increased alanine aminotransferase | 32 | 2.2 | 40 | 1.1
Decreased sodium | 31 | 1.6 | 36 | 0.8
Increased potassium | 29 | 2.5 | 20 | 2.8
Increased aspartate aminotransferase | 27 | 2.2 | 38 | 2
Decreased glucose | 22 | 1.1 | 19 | 1.1
Decreased calcium | 21 | 1.1 | 45 | 3.1

Pheochromocytoma or Paraganglioma

LITESPARK-015

The safety of WELIREG was evaluated in an open-label clinical trial (LITESPARK-015) in 72 patients with locally advanced, unresectable, or metastatic pheochromocytoma or paraganglioma (PPGL) [see Clinical Studies (14.3)]. Patients received WELIREG 120 mg orally once daily until disease progression or unacceptable toxicity.

The median duration of exposure to WELIREG was 20 months (range: 0.3 to 32.5 months).

Serious adverse reactions occurred in 36% of patients who received WELIREG. Serious adverse reactions occurring in ≥2% of patients treated with WELIREG were anemia and hypertension (4.2% each) and pyelonephritis, pneumonia, hypoxia, dyspnea and hemorrhage (2.8% each).

Permanent discontinuation of WELIREG due to adverse reactions occurred in 2 patients (2.8%). Adverse reactions which resulted in permanent discontinuation of WELIREG were increased alanine aminotransferase and paraparesis (1.4% each).

Dosage interruptions of WELIREG due to an adverse reaction occurred in 40% of patients. Adverse reactions which required dosage interruption in >3% of patients were hypoxia, nausea and fatigue (4.2% each).

Dose reductions of WELIREG due to an adverse reaction occurred in 14% of patients. The most frequently reported adverse reaction which required dose reduction was hypoxia (4.2%).

The most common (≥25%) adverse reactions, including laboratory abnormalities, that occurred in patients who received WELIREG were anemia, fatigue, musculoskeletal pain, decreased lymphocytes, increased alanine aminotransferase, increased aspartate aminotransferase, increased calcium, dyspnea, increased potassium, decreased leukocytes, headache, increased alkaline phosphatase, dizziness, and nausea.

Table 6 summarizes the adverse reactions reported in patients treated with WELIREG in LITESPARK-015.

Table 6: Adverse Reactions Occurring in ≥10% of Patients with PPGL Who Received WELIREG in LITESPARK-015
Adverse Reaction | WELIREG (n=72)
Adverse Reaction | All Grades [Graded per NCI CTCAE v5.0] (%) | Grade 3-4 (%)
Blood and Lymphatic
Anemia | 96 | 22
General
Fatigue [Includes other related terms] | 56 | 10
Edema | 24 | 0
Musculoskeletal and Connective Tissue
Musculoskeletal pain | 56 | 6
Muscle spasms | 13 | 0
Muscle weakness | 13 | 2.8
Respiratory, Thoracic, and Mediastinal
Dyspnea | 33 | 1.4
Cough | 15 | 0
Hypoxia | 13 | 10
Nasal congestion | 10 | 0
Nervous System
Headache | 29 | 1.4
Dizziness | 26 | 2.8
Peripheral neuropathy | 13 | 0
Gastrointestinal
Nausea | 25 | 1.4
Constipation | 24 | 1.4
Diarrhea | 15 | 0
Abdominal Pain | 13 | 1.4
Vomiting | 10 | 1.4
Vascular Disorders
Hypertension | 21 | 13
Hypotension | 10 | 2.8
Hemorrhage | 10 | 2.8
Infections
COVID-19 | 17 | 2.8
Metabolism and Nutrition Disorders
Decreased appetite | 14 | 2.8
Investigations
Weight increased | 13 | 7
Cardiac Disorders
Arrhythmia | 11 | 2.8
Palpitations | 10 | 0

Table 7 summarizes the laboratory abnormalities in LITESPARK-015.

Table 7: Select Laboratory Abnormalities (≥20%) That Worsened from Baseline in Patients with PPGL Who Received WELIREG in LITESPARK-015
Laboratory Abnormality | WELIREG (n=72)
Laboratory Abnormality | All Grades % | Grades 3 or 4 %
Hematology
Decreased hemoglobin | 90 | 21
Decreased lymphocytes | 54 | 14
Decreased leukocytes | 30 | 0
Decreased neutrophils | 24 | 1.4
Decreased platelets | 21 | 1.4
Chemistry
Increased ALT | 51 | 4.2
Increased AST | 42 | 4.2
Increased calcium | 34 | 0
Increased potassium | 31 | 2.8
Increased alkaline phosphatase | 25 | 0
Increased creatinine | 24 | 1.4
Decreased sodium | 21 | 0

7 DRUG INTERACTIONS

7.1 Effects of Other Drugs on WELIREG

UGT2B17 or CYP2C19 Inhibitors

Monitor for anemia and hypoxia and reduce the dosage of WELIREG as recommended [see Dosage and Administration (2.2), Warnings and Precautions (5.1, 5.2), Adverse Reactions (6)].

Coadministration of WELIREG with inhibitors of UGT2B17 or CYP2C19 increases belzutifan exposure [see Clinical Pharmacology (12.3, 12.5)], which may increase the risk of adverse reactions of WELIREG.

7.2 Effect of WELIREG on Other Drugs

CYP3A4 Substrates

Avoid coadministration of WELIREG with sensitive CYP3A4 substrates, for which minimal decrease in concentration may lead to therapeutic failures of the substrate. If coadministration cannot be avoided, increase the sensitive CYP3A4 substrate dosage in accordance with its Prescribing Information.

Coadministration of WELIREG with CYP3A4 substrates decreases concentrations of CYP3A substrates [see Clinical Pharmacology (12.3)], which may reduce the efficacy of these substrates. The magnitude of this decrease may be more pronounced in patients who are dual UGT2B17 and CYP2C19 poor metabolizers [see Clinical Pharmacology (12.3)].

Hormonal Contraceptives

Coadministration of WELIREG with hormonal contraceptives may lead to contraceptive failure or an increase in breakthrough bleeding [see Clinical Pharmacology (12.3), Use in Specific Populations (8.3)].

8 USE IN SPECIFIC POPULATIONS

8.1 Pregnancy

Risk Summary

Based on findings in animal studies, WELIREG can cause fetal harm when administered to a pregnant woman. There are no available data on the use of WELIREG in pregnant women to inform the drug-associated risk. In an animal reproduction study, oral administration of belzutifan to pregnant rats during the period of organogenesis caused embryo-fetal lethality, reduced fetal body weight, and fetal skeletal malformations at maternal exposures ≥0.2 times the human exposure (AUC) at the recommended dose of 120 mg daily (see Data). Advise pregnant women and females of reproductive potential of the potential risk to a fetus.

The background risk of major birth defects and miscarriage for the indicated population is unknown. In the U.S. general population, the estimated background risk of major birth defects and miscarriage in clinically recognized pregnancies is 2–4% and 15–20%, respectively.

Data

Animal Data

In a pilot embryo-fetal development study, pregnant rats received oral doses of 6, 60, or 200 mg/kg/day of belzutifan during the period of organogenesis. Belzutifan caused embryo-fetal lethality at doses ≥60 mg/kg/day (approximately 1 time the human exposure at the recommended dose based on AUC). Reduced fetal body weights, fetal rib malformations, and reduced skeletal ossification occurred at doses of 6 and 60 mg/kg/day (approximately ≥0.2 times the human exposure at the recommended dose based on AUC).

8.2 Lactation

Risk Summary

There are no data on the presence of belzutifan or its metabolites in human milk or their effects on the breastfed child or on milk production. Because of the potential for serious adverse reactions in a breastfed child, advise women not to breastfeed during treatment with WELIREG and for 1 week after the last dose.

8.3 Females and Males of Reproductive Potential

WELIREG can cause fetal harm when administered to a pregnant woman [see Use in Specific Populations (8.1)].

Pregnancy Testing

Verify the pregnancy status of females of reproductive potential prior to initiating treatment with WELIREG.

Contraception

Females

Advise females of reproductive potential to use effective non-hormonal contraception during treatment with WELIREG and for 1 week after the last dose. WELIREG can render some hormonal contraceptives ineffective [see Drug Interactions (7.2)].

Males

Advise males with female partners of reproductive potential to use effective contraception during treatment with WELIREG and for 1 week after the last dose.

Infertility

Based on findings in animals, WELIREG may impair fertility in males and females of reproductive potential [see Nonclinical Toxicology (13.1)]. The reversibility of the effect on fertility is unknown.

8.4 Pediatric Use

The safety and effectiveness of WELIREG have been established in pediatric patients aged 12 years and older for the treatment of locally advanced, unresectable, or metastatic pheochromocytoma or paraganglioma. Use of WELIREG in pediatric patients aged 12 years and older is supported by evidence from an adequate and well-controlled study of WELIREG in adults with additional pharmacokinetic data demonstrating that belzutifan exposure is predicted to be within range of that observed in adults, and that the course of locally advanced, unresectable, or metastatic pheochromocytoma or paraganglioma is sufficiently similar in adults and pediatric patients to allow extrapolation of data in adults to pediatric patients [see Clinical Pharmacology (12.3), and Clinical Studies (14.3)].

The safety and effectiveness of WELIREG have not been established in pediatric patients younger than 12 years of age.

8.5 Geriatric Use

Of the 61 patients who received WELIREG for VHL in LITESPARK-004, 3.3% were ≥65 years old [see Clinical Studies (14.1)] Clinical trials of WELIREG in patients with VHL did not include sufficient numbers of patients aged 65 and older to determine whether they respond differently from younger patients.

Of the 372 patients who received WELIREG for advanced RCC in LITESPARK-005, 62% of patients were younger than 65 years, 28% of patients were 65 to 74 years, and 10% were 75 years and over. No overall difference in efficacy was reported between patients who were ≥65 years of age and younger patients. Dose interruptions occurred in 48% of patients ≥65 years of age and in 34% of younger patients. Dose reductions occurred in 18% of patients ≥65 years of age and in 10% of younger patients.

Of the 72 patients who received WELIREG for PPGL in LITESPARK-015, 13% were ≥65 years old and 4.2% were ≥75 years old [see Clinical Studies (14.1)]. Clinical trials of WELIREG in patients with PPGL did not include sufficient numbers of patients aged 65 and older to determine whether they respond differently from younger patients. Other reported clinical experience has not identified differences in responses between the elderly and younger patients.

8.6 Renal Impairment

No dosage modification of WELIREG is recommended in patients with renal impairment including end-stage renal disease. For patients with severe renal impairment (eGFR 15-29 mL/min estimated by MDRD) monitor for increased adverse reactions and modify the dosage as recommended [see Dosage and Administration (2.4), Clinical Pharmacology (12.3)].

8.7 Hepatic Impairment

No dosage modification of WELIREG is recommended in patients with mild [total bilirubin ≤ upper limit of normal (ULN) and aspartate aminotransferase (AST) > ULN or total bilirubin >1 to 1.5 x ULN and any AST] or moderate (total bilirubin within range of >1.5 x ULN and ≤ 3 x ULN and any AST or Child-Pugh B) hepatic impairment. WELIREG has not been studied in patients with severe hepatic impairment (total bilirubin >1.5 x ULN and any AST). For patients with moderate and severe hepatic impairment, monitor for increased adverse reactions and modify the dosage as recommended [see Dosage and Administration (2.4), Clinical Pharmacology (12.3)].

8.8 Dual UGT2B17 and CYP2C19 Poor Metabolizers

Patients who are dual UGT2B17 and CYP2C19 poor metabolizers have higher belzutifan exposures, which may increase the risk of adverse reactions of WELIREG. Monitor for increased adverse reactions in patients who are dual UGT2B17 and CYP2C19 poor metabolizers [see Warnings and Precautions (5), Adverse Reactions (6), Clinical Pharmacology (12.5)].

10 OVERDOSAGE

There is no specific treatment for WELIREG overdose. In cases of suspected overdose, withhold WELIREG and institute supportive care. Grade 3 hypoxia occurred at dosages of 120 mg twice a day and Grade 4 thrombocytopenia occurred at dosages of 240 mg once daily (approximately 2 times the recommended dosage).

11 DESCRIPTION

Belzutifan is an inhibitor of hypoxia-inducible factor-2α (HIF-2α). The chemical name of belzutifan is 3-[[(1S,2S,3R)-2,3-Difluoro-2,3-dihydro-1-hydroxy-7-(methylsulfonyl)-1H-inden-4-yl]oxy]-5-fluorobenzonitrile. The molecular formula is C17H12F3NO4S and the molecular weight is 383.34 Daltons. The chemical structure is:

Belzutifan is a white to light brown powder that is soluble in acetonitrile, dimethoxyethane, and acetone, sparingly soluble in ethyl acetate, very slightly soluble in isopropanol and toluene, and insoluble in water.

WELIREG is supplied as blue, film-coated tablets for oral use containing 40 mg of belzutifan together with croscarmellose sodium, hypromellose acetate succinate, magnesium stearate, mannitol, microcrystalline cellulose, and silicon dioxide, as inactive ingredients. In addition, the film-coating contains FD&C Blue #2 aluminum lake, polyethylene glycol, polyvinyl alcohol, talc, titanium dioxide.

12 CLINICAL PHARMACOLOGY

12.1 Mechanism of Action

Belzutifan is an inhibitor of hypoxia-inducible factor 2 alpha (HIF-2α). HIF-2α is a transcription factor that plays a role in oxygen sensing by regulating genes that promote adaptation to hypoxia. Under normal oxygen levels, HIF-2α is targeted for ubiquitin-proteasomal degradation by VHL protein. Lack of functional VHL protein results in stabilization and accumulation of HIF-2α. Upon stabilization, HIF-2α translocates into the nucleus and interacts with hypoxia-inducible factor 1 beta (HIF-1β) to form a transcriptional complex that induces expression of downstream genes, including genes associated with cellular proliferation, angiogenesis, and tumor growth. Belzutifan binds to HIF-2α, and in conditions of hypoxia or impairment of VHL protein function, belzutifan blocks the HIF-2α-HIF-1β interaction, leading to reduced transcription and expression of HIF-2α target genes. In vivo, belzutifan demonstrated anti-tumor activity in mouse xenograft models of renal cell carcinoma.

12.2 Pharmacodynamics

Reductions in plasma levels of erythropoietin (EPO) were observed to be dose- and exposure-dependent at dosages up to 120 mg once daily. The maximum EPO suppression occurred following 2 weeks of consecutive dosing of WELIREG (mean percent decrease from baseline of approximately 60%). Mean EPO levels gradually returned to baseline values after 12 weeks of treatment.

The incidence of Grade 3 anemia increased with higher belzutifan exposure in patients with baseline hemoglobin levels <12 g/dL [see Warnings and Precautions (5.1)].

Cardiac Electrophysiology

At the recommended dosage, WELIREG does not cause large mean increases (i.e., >20 msec) in the QT interval.

12.3 Pharmacokinetics

The Cmax and AUC of belzutifan increase proportionally over a dose range of 20 mg to 120 mg (0.17 to 1 times the approved recommended dose). The estimated geometric mean steady-state (CV%) Cmax is 1.5 μg/mL (45%) and AUC0-24h is 20 μg•hr/mL (62%) . Steady state is reached after approximately 3 days.

Absorption

The median Tmax occurs at 1 to 2 hours after WELIREG administration.

Effect of Food

A high-fat, high-calorie meal (total calories approximately 1000 kcal, 56 g fat, 55 g carbohydrate, and 31 g protein) delayed Tmax by approximately 2 hours with no clinically significant effect on Cmax and AUC of belzutifan.

Distribution

The estimated mean (CV%) volume of distribution is 119 L (28%) Plasma protein binding of belzutifan is 45%. The blood-to-plasma concentration ratio of belzutifan is 0.88.

Elimination

The estimated mean (CV%) clearance is 6 L/hr (58%) and the mean elimination half-life is 14 hrs.

Metabolism

Belzutifan is primarily metabolized by UGT2B17 and CYP2C19 and to a lesser extent by CYP3A4 [see Clinical Pharmacology (12.5)].

Excretion

Following a single oral dose of radiolabeled belzutifan , approximately 49.6% of the dose was excreted in urine and 51.7% in feces (primarily as inactive metabolites).

Specific Populations

Patients who are poor metabolizers of UGT2B17 and CYP2C19 had higher belzutifan AUC [see Clinical Pharmacology (12.5)].

No clinically significant differences in the pharmacokinetics of belzutifan were observed based on age (15 to 90 years), sex, ethnicity (non-Hispanic, Hispanic), race (White (76%), Black (5%), Asian (15%), Native American, Pacific Islander), or body weight (40 to 166 kg).

Pediatric patients

The exposure of belzutifan in pediatric patients 12 years and older is predicted to be within range of that observed in adults at the recommended dosage.

Patients with Renal Impairment

No clinically significant differences in the mean belzutifan exposure were observed between subjects with normal renal function and those with mild (eGFR 60-89 mL/min) or moderate renal impairment (GFR 30-59 mL/min) and those with end-stage renal disease (eGFR <15 mL/min) requiring dialysis.

Patients with Hepatic Impairment

No clinically significant differences in the mean belzutifan exposure were observed between subjects with normal liver function (total bilirubin and AST ≤ ULN), and those with mild hepatic impairment (total bilirubin ≤ ULN and AST > ULN or total bilirubin >1 to 1.5 x ULN and any AST). Belzutifan exposure (AUC) increased by 1.5-fold in patients with moderate hepatic impairment (Child-Pugh B) compared to subjects with normal hepatic function. Patients with severe hepatic impairment have not been studied.

Drug Interaction Studies

Clinical Studies and Model-Informed Approaches

Effect of Belzutifan on CYP3A Substrates: Coadministration of WELIREG 120 mg once daily with midazolam (a sensitive CYP3A4 substrate) decreased the midazolam AUC by 40% and the Cmax by 34%. Midazolam AUC is predicted to decrease up to 70% in patients with higher belzutifan concentrations (e.g., dual poor metabolizers) [see Clinical Pharmacology (12.5)].

In Vitro Studies

Cytochrome P450 (CYP) Enzymes: Belzutifan does not inhibit CYP1A2, CYP2B6, CYP2C8, CYP2C9, CYP2C19, CYP2D6, or CYP3A4.

Belzutifan does not induce CYP1A2 or CYP2B6.

Transporter Systems: Belzutifan is a substrate of P-gp, OATP1B1, and OATP1B3, but is not a substrate of BCRP.

Belzutifan inhibits MATE2K. Belzutifan does not inhibit P-gp, BCRP, OATP1B1, OATP1B3, OAT1, OAT3, OCT2, or MATE1.

12.5 Pharmacogenomics

Patients who are UGT2B17, CYP2C19, or dual UGT2B17 and CYP2C19 poor metabolizers are estimated to have 2.5-, 1.3-, or 3.2-fold higher belzutifan steady state AUC0-24h, respectively compared to patients who are UGT2B17 normal (extensive) metabolizers and CYP2C19 non-poor (ultrarapid, rapid, normal, and intermediate) metabolizers [see Use in Specific Populations (8.8)].

UGT2B17 poor metabolizers who are homozygous for the UGT2B17*2 allele have no UGT2B17 enzyme activity. CYP2C19 poor metabolizers (such as *2/*2, *3/*3, *2/*3) have significantly reduced or absent CYP2C19 enzyme activity. Approximately 15% of White, 6% of Black or African American, and up to 77% of certain Asian populations are UGT2B17 poor metabolizers. Approximately 2% of White, 5% of Black or African American, and up to 19% of certain Asian populations are CYP2C19 poor metabolizers. Approximately 0.4% of White, 0.3% of Black or African American, and up to 15% of certain Asian populations are dual UGT2B17 and CYP2C19 poor metabolizers.

13 NONCLINICAL TOXICOLOGY

13.1 Carcinogenesis, Mutagenesis, Impairment of Fertility

Carcinogenicity studies have not been conducted with belzutifan.

Belzutifan was not mutagenic in the in vitro bacterial reverse mutation (Ames) assay. Belzutifan was not clastogenic in either an in vitro micronucleus assay or an in vivo rat bone marrow micronucleus assay.

Fertility studies in animals have not been conducted with belzutifan. In repeat-dose toxicity studies up to 3-month duration, belzutifan-related findings included degeneration/atrophy of testes and hypospermia and cellular debris of the epididymis in rats administered ≥2 mg/kg/day (approximately 0.1 times the human exposure at the recommended dose of 120 mg daily). Findings in testes and epididymis were associated with decreased sperm count and motility and abnormal sperm morphology at ≥6 mg/kg/day (approximately 0.2 times the human exposure at the recommended dose of 120 mg daily) and did not reverse by the end of the recovery period. Belzutifan had no adverse effects on female reproductive organs in repeat-dose toxicity studies up to 3-month duration; however, belzutifan caused embryo-fetal lethality (post-implantation loss) in pregnant rats given oral doses ≥60 mg/kg/day (approximately 1 time the human exposure at the recommended dose based on AUC) during the period of organogenesis [see Use in Specific Population (8.1)].

14 CLINICAL STUDIES

14.1 von Hippel-Lindau (VHL) disease

The efficacy of WELIREG was evaluated in LITESPARK-004 (NCT03401788), an open-label clinical trial in 61 patients with VHL-associated RCC diagnosed based on a VHL germline alteration and with at least one measurable solid tumor localized to the kidney as defined by response evaluation criteria in solid tumors (RECIST) v1.1. Enrolled patients had other VHL-associated tumors including CNS hemangioblastomas and pNET. CNS hemangioblastomas and pNET in these patients were diagnosed based on the presence of at least one measurable solid tumor in brain/spine or pancreas, respectively, as defined by RECIST v1.1 and identified by IRC. The study excluded patients with metastatic disease. Patients received WELIREG 120 mg orally once daily until disease progression or unacceptable toxicity.

The study population characteristics were: median age 41 years [range 19-66 years], 3.3% age 65 or older; 53% male; 90% were White, 3.3% were Black or African-American, 1.6% were Asian, and 1.6% were Native Hawaiian or other Pacific Islander; 82% had an ECOG PS of 0, 16% had an ECOG PS of 1, and 1.6% had an ECOG PS of 2; and 84% had VHL Type I Disease. The median diameter of RCC target lesions per central independent review committee (IRC) was 2.2 cm (range 1-6.1). Median time from initial radiographic diagnosis of VHL-associated RCC tumors that led to enrollment on LITESPARK-004 to the time of treatment with WELIREG was 17.9 months (range 2.8-96.7). Seventy-seven percent of patients had prior surgical procedures for RCC.

The major efficacy endpoint for the treatment of VHL-associated RCC was objective response rate (ORR) measured by radiology assessment using Response Evaluation Criteria In Solid Tumors (RECIST) v1.1 as assessed by IRC. Additional efficacy endpoints included duration of response (DoR), and time to response (TTR).

Table 8 summarizes the efficacy results for VHL-associated RCC in LITESPARK-004.

Table 8: Efficacy Results (IRC assessment) for LITESPARK-004 for VHL-Associated RCC
Efficacy Outcome Measure | WELIREG n=61
Objective Response Rate, % (n) (95% CI) | 49% (30) [All patients with a response were followed for a minimum of 18 months from the start of treatment.] (36, 62)
Complete response | 0%
Partial response | 49%
Duration of Response
Median in months (range) | Not reached (2.8+, 22+)
% (n) with DoR ≥ 12 months | 56% (17/30)
+ Denotes ongoing response.

For VHL-associated RCC, median TTR was 8 months (range 2.7, 19).

Table 9 summarizes the efficacy results for VHL-associated pNET or CNS hemangioblastomas in LITESPARK-004.

Table 9. Efficacy Results (IRC assessment) for LITESPARK-004 for VHL-Associated Subgroups with CNS Hemangioblastomas or pNET
Endpoint | Patients with CNS Hemangioblastomas n=24 [Number of patients with measurable solid lesions, based on IRC assessment.] | Patients with pNET n=12
Objective Response Rate, % (n) (95% CI) | 63%, (15) (41, 81) | 83% (10) (52, 98)
Complete response | 4% (1) | 17% (2)
Partial response | 58% (14) | 67% (8)
Duration of Response
Median in months (range) | Not reached (3.7+, 22+) | Not reached (11+, 19+)
% (n) with DoR ≥12 months | 73% (11/15) | 50% (5/10)
+ Denotes ongoing response.

For VHL-associated CNS hemangioblastomas, TTR was 3.1 months (range 2.5, 11). For VHL-associated pNET, median TTR was 8.1 months (range 2.7, 11).

Decreases in size of CNS hemangioblastoma-associated peri-tumoral cysts and syringes were observed.

14.2 Advanced Renal Cell Carcinoma (RCC)

The efficacy of WELIREG was evaluated in LITESPARK-005 (NCT04195750), an open-label, randomized, active-controlled clinical trial in 746 patients with unresectable, locally advanced or metastatic clear cell RCC that progressed following PD-1 or PD-L1 checkpoint inhibitor and VEGF receptor targeted therapies either in sequence or in combination.

Patients could have received up to 3 prior treatment regimens and were required to have measurable disease per RECIST v1.1. Patients were randomized in a 1:1 ratio to receive 120 mg WELIREG or 10 mg everolimus orally once daily until disease progression or unacceptable toxicity. Randomization was stratified by IMDC risk categories (favorable versus intermediate versus poor) and number of prior VEGF receptor targeted therapies (1 versus 2-3). Patients were evaluated radiologically at Week 9 from the date of randomization, then every 8 weeks through Week 49, and every 12 weeks thereafter.

The study population characteristics were: median age 63 years [range 22 to 90 years], 42% age 65 or older; 78% male; 79% White; 12% Asian; 1% Black or African American; 11% Hispanic or Latino; 44% ECOG performance status 0 and 55% ECOG performance status 1. Prior therapies: 13% patients had 1 prior line of therapy, 43% had 2 prior lines of therapy and 43% had 3 prior lines of therapy; 49% received 2 to 3 prior VEGF receptor targeted therapies. Patient distribution by IMDC risk categories was 22% favorable, 66% intermediate, and 12% poor. Common sites of metastasis in patients were 65% lung, 59% lymph nodes, and 49% bone.

The major efficacy endpoints were Progression Free Survival (PFS) measured by BICR using RECIST v1.1 and Overall Survival (OS). Additional efficacy endpoint included objective response rate (ORR) by BICR using RECIST v1.1.

The trial demonstrated a statistically significant improvement in PFS for patients randomized to WELIREG compared with everolimus. Table 10 and Figure 1 summarize the efficacy results for LITESPARK-005.

Table 10: Efficacy Results for Advanced RCC (IRC assessment) for LITESPARK-005
Efficacy Outcome Measure | WELIREG n=374 | Everolimus n=372
Progression-Free Survival (PFS)
Number of events, n (%) | 257 (69%) | 262 (70%)
Progressive disease | 234 (63%) | 222 (60%)
Death | 23 (6%) | 40 (11%)
Median in months (95% CI) [From product-limit (Kaplan-Meier) method for censored data] | 5.6 (3.9, 7.0) | 5.6 (4.8, 5.8)
Hazard ratio [Based on the stratified Cox proportional hazard model.] (95% CI) | 0.75 (0.63, 0.90)
p-Value [One-sided p-Value based on stratified log-rank test compared with the significance boundary of 0.0021.] | 0.0008
Overall Survival (OS)
Number of events, n (%) | 254 (68%) | 259 (70%)
Median in months (95% CI) | 21 (18, 24) | 18 (16, 22)
Hazard ratio (95% CI) | 0.92 (0.77, 1.10)
p-Value [Based on stratified log-rank test.] | NS
Confirmed Objective Response Rate
Number of patients with measurable disease at baseline | 373 | 364
ORR % (n) (95% CI) | 22% (82) (18, 27) | 4% (13) (2, 6)
Complete response | 3% (10) | 0% (0)
Partial response | 19% (72) | 4% (13)
p-Value [One-sided p-value based on stratified Miettinen and Nurminen (M&N) method.] | <0.0001
NS – not statistically significant

Among the 82 patients treated with WELIREG who achieved a confirmed response based on BICR per RECIST 1.1, 25 (30%) patients had a duration of response ≥12 months.

Figure 1: Kaplan-Meier Curve for Progression-Free Survival in LITESPARK-005

14.3 Pheochromocytoma or Paraganglioma

The efficacy of WELIREG was evaluated in LITESPARK-015 (NCT04924075), an open-label, multi-cohort clinical trial in 72 patients in Cohort A1 who had measurable disease verified by BICR per RECIST v1.1, documented histopathological diagnosis of pheochromocytoma or paraganglioma (PPGL), locally advanced or metastatic disease that was not amenable to surgery or curative treatment, and adequately controlled blood pressure (defined as BP <150/90 mm Hg, <135/85 mm Hg for adolescents) with no change in antihypertensive medications for patients with concomitant hypertension for at least 2 weeks prior to start of study treatment. Patients with carcinomatous meningitis were excluded. Patients received WELIREG 120 mg orally once daily until disease progression or unacceptable toxicity.

The study population characteristics were: median age 52 years [range 22 to 77 years], 13% age 65 or older; 58% male; 93% White; 4.2% Black or African-American; 1.4% Asian; 6% Hispanic or Latino; 54% had an ECOG PS of 0 and 46% had an ECOG PS of 1. The median number of prior therapies was 1: (range: 0 to 5). A total of 50% of patients received prior chemotherapy, 44% received prior radiopharmaceuticals, and 25% received prior VEGF-TKIs. No patients had a history of VHL disease.

The major efficacy outcome measure for the treatment of locally advanced PPGL was objective response rate (ORR) measured by BICR using RECIST v1.1. Additional efficacy outcome measures were duration of response (DOR), time to response (TTR), and the proportion of patients who had a reduction in at least one antihypertensive medication by at least 50% maintained for at least six months.

Table 11 summarizes the efficacy results for PPGL in LITESPARK-015.

Table 11: Efficacy Results in Patients with PPGL in LITESPARK-015
Efficacy Outcome Measure | WELIREG n=72
Confirmed Objective Response Rate [Based on BICR.] , [All responses were partial responses.]
ORR, % (95% CI) | 26% (17, 38)
Duration of Response
Median in months (95% CI) [Based on Kaplan-Meier estimates.] | 20.4 (8.3, NR)
Range | 5.6+, 29.6+
% with duration ≥ 12 months | 53%
Reduction in at least one antihypertensive medication by at least 50% maintained for at least 6 months
Number of patients | 19
Proportion of patients (95% CI [Calculated using the Clopper-Pearson method.]) [Based on the number of patients who were on antihypertensive medications at baseline (N=60).] | 32% (20, 45)
NR = not reached
+ = Denotes ongoing response.
Data cut-off: October 23, 2024

For PPGL, the median TTR was 11.0 months (range 1.7 to 24.8).

16 HOW SUPPLIED/STORAGE AND HANDLING

How Supplied

WELIREG tablets are supplied as 40 mg blue, oval shaped, film-coated, debossed with “177” on one side and plain on the other side, available in:

- bottles of 90 tablets with child-resistant closure: NDC 0006-5331-01.

The bottle also contains two desiccant canisters. Do not eat.

Storage and Handling

Store at 20°C to 25°C (68°F to 77°F), excursions permitted between 15°C and 30°C (59°F and 86°F) [see USP Controlled Room Temperature].

17 PATIENT COUNSELING INFORMATION

Advise the patient to read the FDA-approved patient labeling (Medication Guide).

Anemia

Inform patients that WELIREG can cause severe anemia that may require blood transfusions and that red blood cell levels will be monitored routinely during treatment. Advise patients to contact their healthcare provider if the patient experiences any symptoms suggestive of anemia [see Warnings and Precautions (5.1)].

Hypoxia

Inform patients that WELIREG can cause severe hypoxia that may require discontinuation, supplemental oxygen, or hospitalization; and that oxygen levels will be monitored routinely during treatment. Advise patients to contact their healthcare provider if the patient experiences any symptoms suggestive of hypoxia [see Warnings and Precautions (5.2)].

Embryo-Fetal Toxicity

- Advise pregnant women and females of reproductive potential of the risk to a fetus. Advise females to inform their healthcare provider of a known or suspected pregnancy [see Warnings and Precautions (5.3) and Use in Specific Population (8.1)].
- Advise females of reproductive potential to use effective non-hormonal contraception during treatment with WELIREG and for 1 week after the last dose [see Use in Specific Populations (8.3)].
- Advise male patients with female partners of reproductive potential to use effective contraception during treatment with WELIREG and for 1 week after the last dose [see Use in Specific Populations (8.3)].

Lactation

Advise females not to breastfeed during treatment with WELIREG and for 1 week after the last dose [see Use in Specific Populations (8.2)].

Infertility

Advise male and female patients that WELIREG may impair fertility [see Use in Specific Populations (8.3)].

Dosage and Administration

Instruct patients to take their dose of WELIREG at the same time each day (once daily). Advise patients WELIREG can be taken with or without food. Each tablet should be swallowed whole [see Dosage and Administration (2.1)].

Manufactured for: Merck Sharp & Dohme LLC
Rahway, NJ 07065, USA

For patent information: www.msd.com/research/patent

Copyright © 2021-2025 Merck & Co., Inc., Rahway, NJ, USA, and its affiliates.
All rights reserved.

uspi-mk6482-t-2505r004

MEDICATION GUIDE
WELIREG® (Well-ih-reg)
(belzutifan)
tablets

What is the most important information I should know about WELIREG?
WELIREG may cause serious side effects, including:

- Low red blood cell counts (anemia). Low red blood cell counts are common with WELIREG and can be severe. You may need a blood transfusion if your red blood cell counts drop too low. Your healthcare provider will do blood tests to check your red blood cell counts before you start and during treatment with WELIREG. Tell your healthcare provider if you get any symptoms of low red blood cell counts, including tiredness, feeling cold, shortness of breath, chest pain, or fast heartbeat.
- Low oxygen levels in your body. WELIREG can cause low oxygen levels in your body that can be severe and may require you to stop treatment with WELIREG, receive oxygen therapy, or be hospitalized. Your healthcare provider will monitor your oxygen levels before you start and during treatment with WELIREG. Tell your healthcare provider or get medical help right away if you get symptoms of low oxygen in your body, including shortness of breath or increased heart rate.
- Harm to your unborn baby. Treatment with WELIREG during pregnancy can cause harm to your unborn baby.
  Females who are able to become pregnant:
  - Your healthcare provider will do a pregnancy test before you start treatment with WELIREG.
  - You should use an effective form of non-hormonal birth control (contraception) during treatment with WELIREG and for 1 week after your last dose.
  - Birth control methods that contain hormones (such as birth control pills, injections, or transdermal system patches) may not work as well during treatment with WELIREG.
  - Talk to your healthcare provider about birth control methods that may be right for you during treatment with WELIREG.
  - Tell your healthcare provider right away if you become pregnant or think you may be pregnant during treatment with WELIREG.
    Males with female partners who are able to become pregnant:
  - You should use effective birth control (contraception) during treatment with WELIREG and for 1 week after your last dose.
  - Tell your healthcare provider right away if your partner becomes pregnant or thinks she is pregnant while you are taking WELIREG.

See “What are the possible side effects of WELIREG?” for more information about side effects.

What is WELIREG?

WELIREG is a prescription medicine used to treat:

- von Hippel-Lindau (VHL) disease in adults who need treatment for a type of kidney cancer called renal cell carcinoma (RCC), tumors in the brain and spinal cord called central nervous system hemangioblastomas (CNS), or a type of pancreatic cancer called pancreatic neuroendocrine tumors (pNET), that do not require surgery right away.
- a type of kidney cancer called RCC with a clear cell component in adults that has spread (advanced RCC) following treatment with a programmed death-receptor-1 (PD-1) or programmed death-ligand 1 (PD-L1) inhibitor and vascular endothelial growth factor tyrosine kinase inhibitor (VEGF-TKI) cancer medicines.
- neuroendocrine tumors called pheochromocytoma or paraganglioma (PPGL) in adults and children 12 years of age and older that have spread to areas near the adrenal glands (locally advanced), or cannot be removed by surgery (unresectable), or that has spread to other parts of the body (metastatic).

It is not known if WELIREG is safe and effective in children younger than 12 years of age.

Before taking WELIREG, tell your healthcare provider about all of your medical conditions, including if you:

- have low red blood cell counts (anemia)
- are pregnant or plan to become pregnant. See “What is the most important information I should know about WELIREG?”
- are breastfeeding or plan to breastfeed. It is not known if WELIREG passes into your breast milk. Do not breastfeed during treatment with WELIREG and for 1 week after your last dose.

Tell your healthcare provider about all the medicines you take, including prescription and over-the-counter medicines, vitamins, and herbal supplements.
Taking WELIREG with certain other medicines can affect each other and cause serious side effects.

Know the medicines you take. Keep a list of them to show to your healthcare provider and pharmacist when you get a new medicine.

How should I take WELIREG?

- Take WELIREG exactly as your healthcare provider tells you.
- Do not stop taking WELIREG or change your dose without talking to your healthcare provider.
- Take your prescribed dose of WELIREG 1 time a day, at the same time each day.
- Your healthcare provider may change your dose, temporarily stop, or permanently stop treatment with WELIREG if you have certain side effects.
- Take WELIREG with or without food.
- Swallow WELIREG tablets whole. Do not chew, crush, or split WELIREG tablets.
- If you miss a dose of WELIREG, take it as soon as possible on the same day. Then take your next dose of WELIREG at your regular time the next day. Do not take extra tablets to make up for the missed dose.
- If you vomit after taking a dose of WELIREG, do not take an extra dose. Take your next dose at your regular time the next day.
- If you take too much WELIREG, call your healthcare provider or go to the nearest emergency room right away.

What are the possible side effects of WELIREG?

WELIREG may cause serious side effects, including:

- See “What is the most important information I should know about WELIREG?”

The most common side effects of WELIREG in adults with VHL disease include:

- tiredness
- increased creatinine (kidney function test)
- headache

- dizziness
- increased blood sugar (glucose) levels
- nausea

The most common side effects of WELIREG in adults with advanced RCC include:

- tiredness
- decreased white blood cells
- increased creatinine (kidney function test)
- muscle and joint pain

- increased liver function tests
- decreased blood salts (sodium) levels
- increased blood potassium levels

The most common side effects of WELIREG in adults with PPGL include:

- tiredness
- muscle and joint pain
- decreased white blood cells
- increased liver function tests
- increased blood calcium levels

- shortness of breath
- increased blood potassium levels
- headache
- dizziness
- nausea

WELIREG may cause fertility problems in males and females, which may affect your ability to have children. Talk to your healthcare provider if this is a concern for you.

These are not all of the possible side effects of WELIREG.
Call your doctor for medical advice about side effects. You may report side effects to FDA at 1-800-FDA-1088.

How should I store WELIREG?

- Store WELIREG at room temperature between 68°F to 77°F (20°C to 25°C).
- The WELIREG bottle has a child-resistant closure.
- The WELIREG bottle contains 2 desiccant canisters that help keep your medicine dry. Do not eat the desiccant canisters.

Keep WELIREG and all medicines out of the reach of children.

General information about the safe and effective use of WELIREG.

Medicines are sometimes prescribed for purposes other than those listed in a Medication Guide. Do not use WELIREG for a condition for which it was not prescribed. Do not give WELIREG to other people, even if they have the same symptoms that you have. It may harm them. You can ask your pharmacist or healthcare provider for information about WELIREG that is written for health professionals.

What are the ingredients in WELIREG?

Active ingredient: belzutifan

Inactive ingredients: croscarmellose sodium, hypromellose acetate succinate, magnesium stearate, mannitol, microcrystalline cellulose, and silicon dioxide. The film-coating contains FD&C Blue #2 aluminum lake, polyethylene glycol, polyvinyl alcohol, talc, and titanium dioxide.

Manufactured for: Merck Sharp & Dohme LLC
Rahway, NJ 07065, USA

For patent information: www.msd.com/research/patent

Copyright © 2021-2025 Merck & Co., Inc., Rahway, NJ, USA, and its affiliates.
All rights reserved.

usmg-mk6482-t-2505r005

This Medication Guide has been approved by the U.S. Food and Drug Administration.

Revised: 05/2025

PRINCIPAL DISPLAY PANEL - 40 mg Bottle Label

NDC 0006-5331-01

Welireg®
(belzutifan) tablets

40 mg

Dispense the accompanying Medication
Guide to each patient.

Each tablet contains 40 mg of belzutifan.

Rx only

90 Tablets